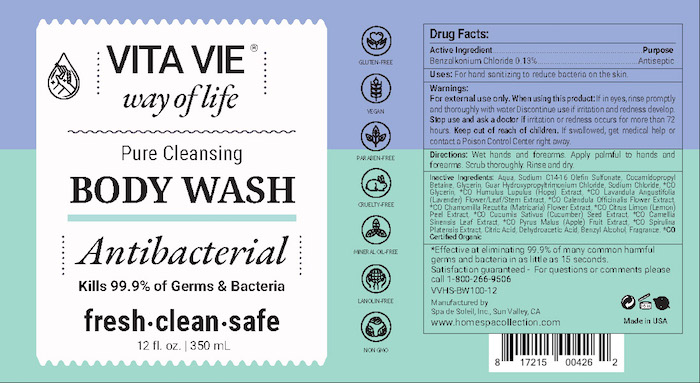 DRUG LABEL: Vita Vie Antibacterial Wash
NDC: 68062-2217 | Form: SOLUTION
Manufacturer: Spa De Soleil
Category: otc | Type: HUMAN OTC DRUG LABEL
Date: 20200616

ACTIVE INGREDIENTS: BENZALKONIUM CHLORIDE 0.455 g/350 mL
INACTIVE INGREDIENTS: WATER; GLYCERIN

Vita Vie Antibacterial Wash

Active Ingredient - Benzalkonium Chloride 0.13%

Purpose - Antispetic Handwash

PURPOSE

Uses - For washing to decrease bacteria on the skin

Warnings - For external use only

When using this product avoid contact with eyes. In case of eye contact, rinse promptly and thoroughly with water.

Stop use and ask a doctor if irritation and redness occurs for more than 72 hours.

Keep out of reach of children. If swallowed, get medical help or contact a Poison Control Center right away.

INDICATIONS AND USAGE

Directions: We hands and forearms. Apply a palmful of foam to hands and lather over hands and forearms. Scrub thoroughly. Rinse and dry.

DOSAGE AND ADMINISTRATION

Repeat applications as needed.

INACTIVE INGREDIENT

Inactive Ingredients: Aqua, Sodium C14-16 Olefin Sulfonate, Cocamidopropyl Betaine, Glycerin, Guar Hydroxypropyltrimonium Chloride, Sodium Chloride, *CO Glycerin, *CO Humulus Lupulus (Hops) Extract, *CO Lavandula Angustifolia (Lavender) Flower/Leaf/Stem Extract, *CO Calendula Officinalis Flower Extract, *CO Chamomilla Recutita (Matricaria) Flower Extract, *CO Citrus Limon (Lemon) Peel Extract, *CO Cucumis Sativus (Cucumber) Seed Extract, *CO Camellia Sinensis Leaf Extract, *CO Pyrus Malus (Apple) Fruit Extract, *CO Spirulina Platensis Extract, Citric Acid, Dehydroacetic Acid, Benzyl Alcohol, Fragrance